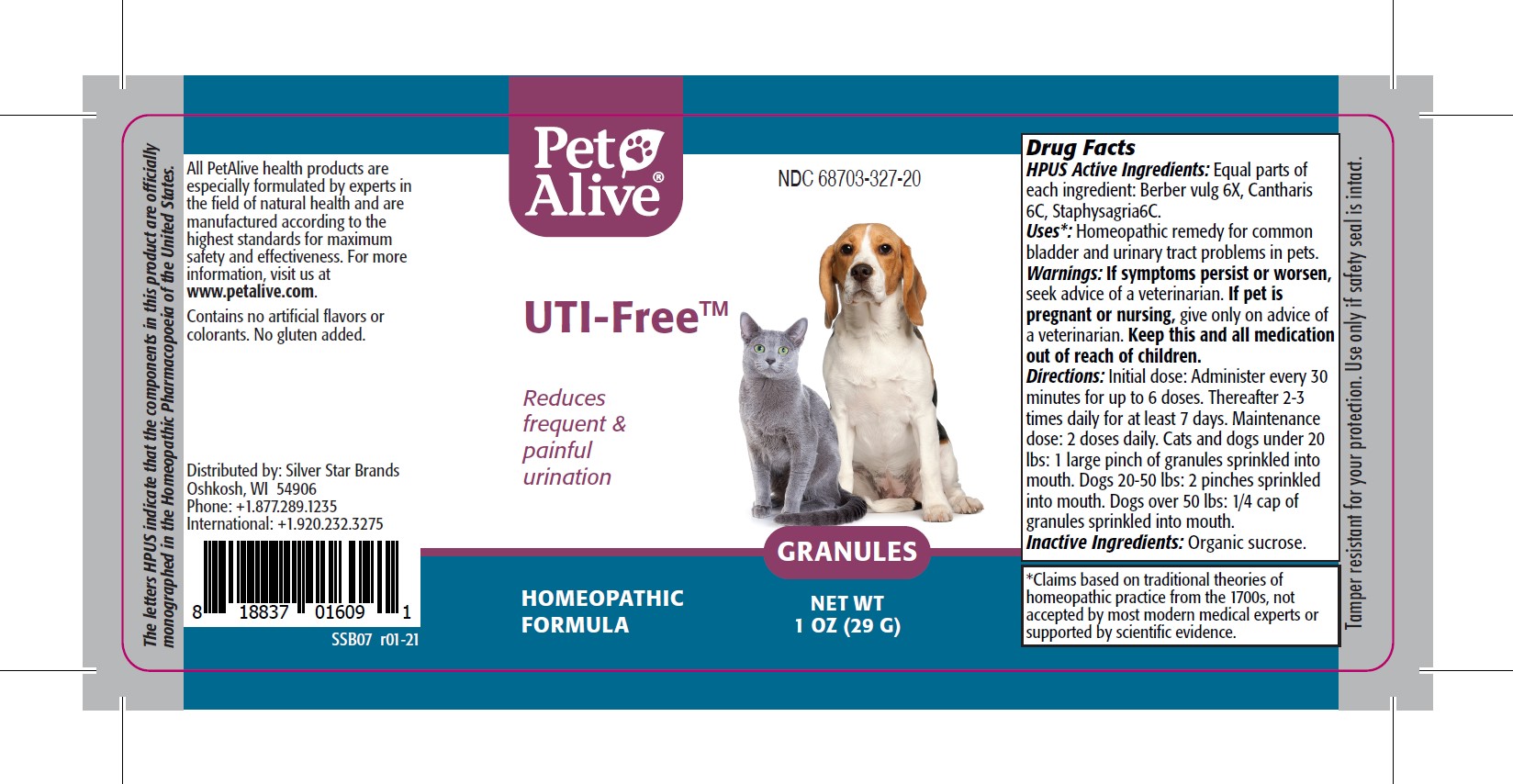 DRUG LABEL: PetAlive UTI-Free
NDC: 68703-327 | Form: GRANULE
Manufacturer: SILVER STAR BRANDS
Category: homeopathic | Type: OTC ANIMAL DRUG LABEL
Date: 20251216

ACTIVE INGREDIENTS: BERBERIS VULGARIS ROOT BARK 6 [hp_X]/26.67 mg; LYTTA VESICATORIA 6 [hp_C]/26.67 mg; DELPHINIUM STAPHISAGRIA SEED 6 [hp_C]/26.67 mg
INACTIVE INGREDIENTS: sucrose

PetAlive UTI-Free

PURPOSE

Reduces frequent and painful urination

HPUS Active Ingredients:

Berber vulg 6X
Cantharis 6C
Staphysagria 6C

INDICATIONS AND USAGE

Uses: Homeopathic remedy for common bladder and urinary tract problems in pets.

WARNINGS

Warnings: If symptoms persist or worsen, seek advice of a veterianrian

PREGNANCY OR BREAST FEEDING

If pregnant or nursing, give only on advice of a veterinarian

KEEP OUT OF REACH OF CHILDREN

Keep this and all medication out of reach of children.

DOSAGE AND ADMINISTRATION

Directions: Directions: Initial dose: Administer every 30 minutes for up to 6 doses. Thereafter 2-3 times daily for at least 7 days. Maintenance dose: 2 doses daily. Cats and dogs under 20 lbs: 1 large pinch of granules sprinkled into mouth. Dogs 20-50 lbs: 2 pinches sprinkled into mouth. Dogs over 50 lbs: 1/4 cap of granules sprinkled into mouth.

Inactive Ingredients: Organic sucrose

INFORMATION FOR OWNERS/CAREGIVERS

The letters HPUS indicate that the components in this product are officially monographed in the Homeopathic Pharmacopoeia of the United States.

All PetAlive health products are especially formulated by experts in the field of natural health and are manufactured according to the highest standards for maximum safety and effectiveness. For more information, visit us at www.petalive.com.

Contains no artificial flavors or colorants. No gluten added.

Distributed by: Silver Star Brands
Oshkosh, WI 54906
Phone: +1.877.289.1235
International: +1.920.232.3275

STORAGE AND HANDLING

Tamper resistant for your protection. Use only if safety seal is intact.